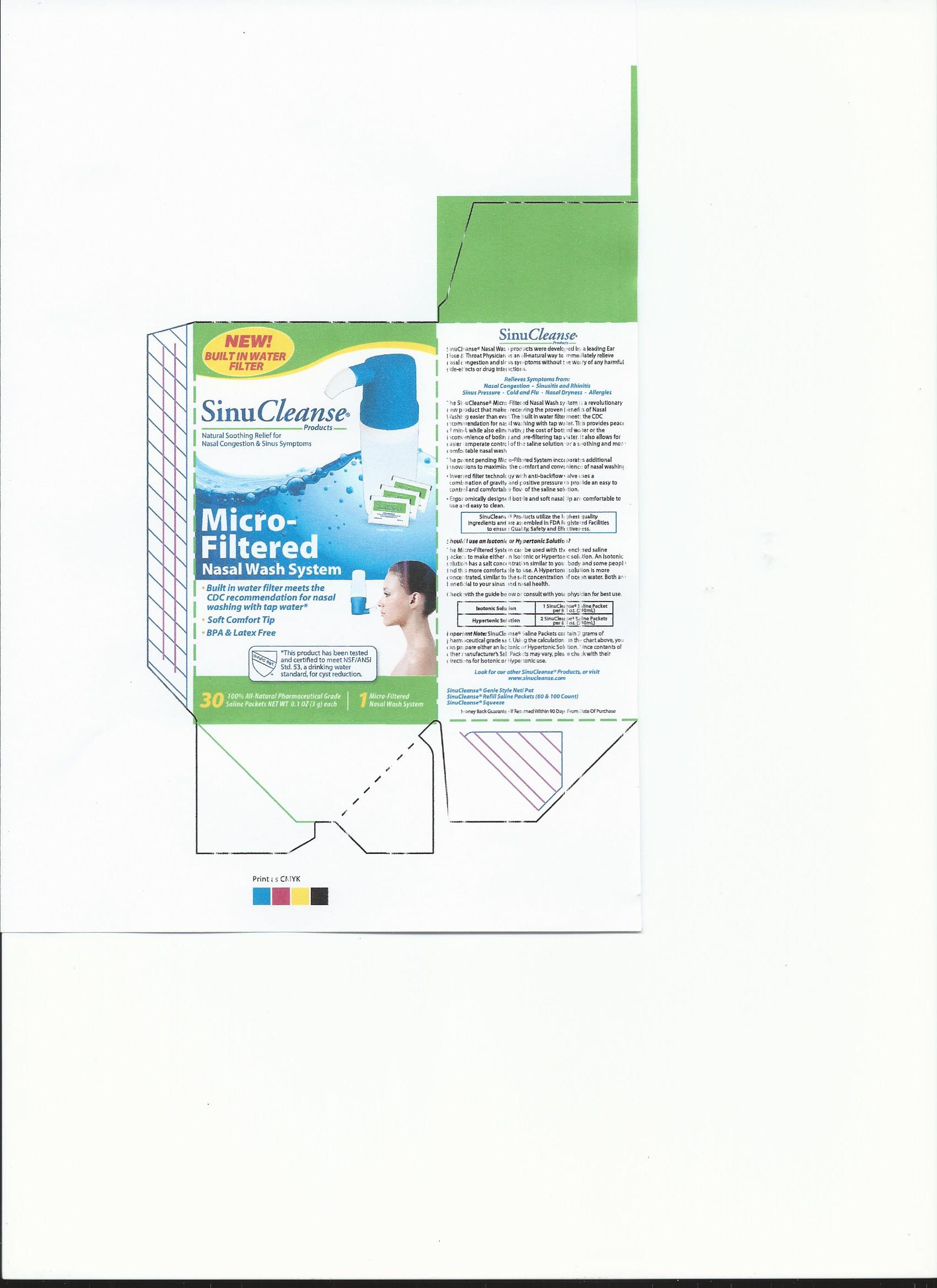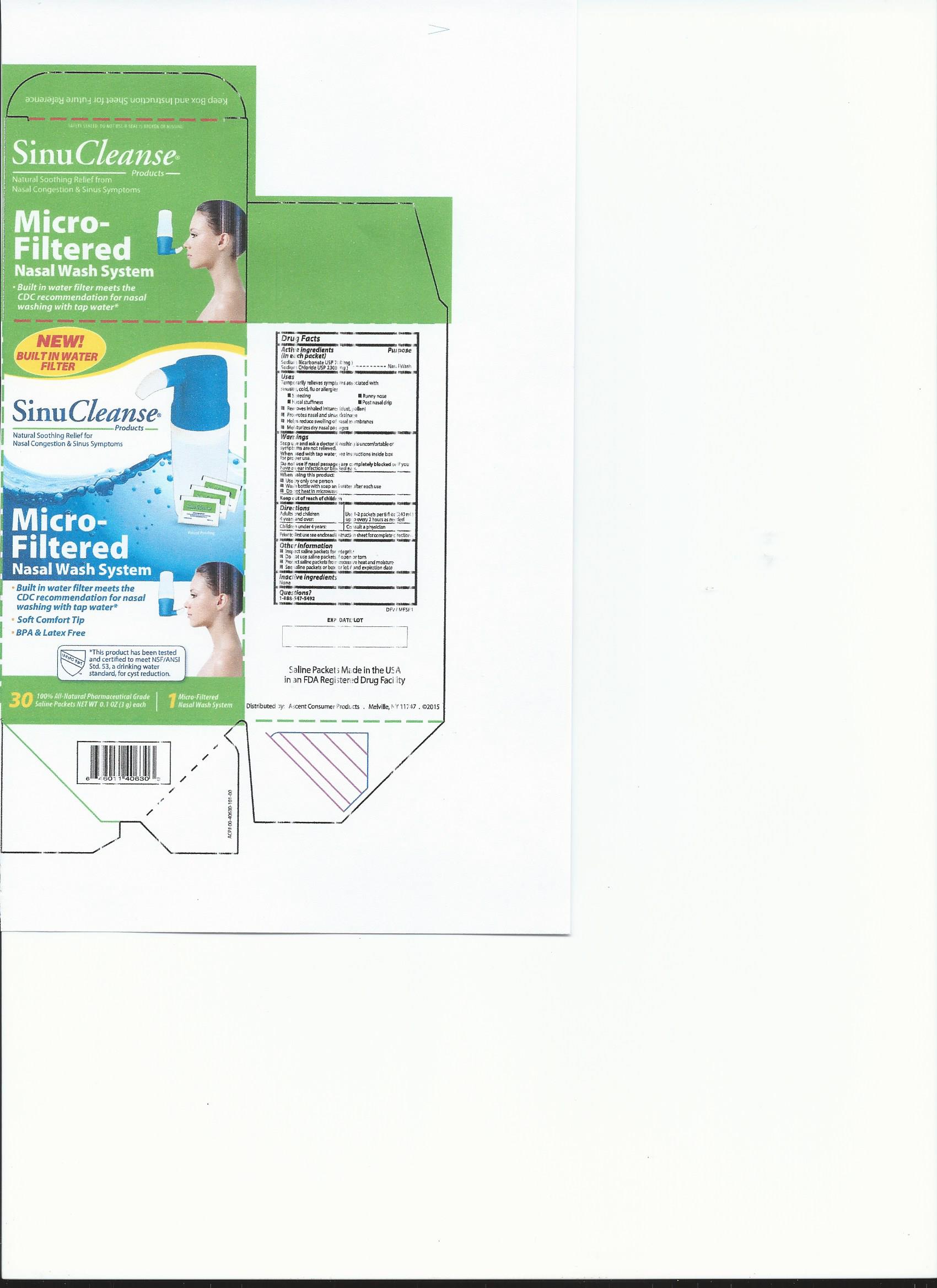 DRUG LABEL: SinuCleanse Micro-Filtered Nasal Wash System
NDC: 42829-406 | Form: KIT | Route: NASAL
Manufacturer: ASCENT CONSUMER PRODUCTS, INC.
Category: otc | Type: HUMAN OTC DRUG LABEL
Date: 20250701

ACTIVE INGREDIENTS: SODIUM BICARBONATE 700 mg/3000 mg; SODIUM CHLORIDE 2300 mg/3000 mg
INACTIVE INGREDIENTS: WATER

Active ingredients

(in each packet)

Sodium Bicarbonate USP 700 mg

Sodium Chloride USP 2300 mg

Purpose

Nasal Wash

Uses

Temporarily relieves symptoms associated with

sinusitis, cold, flu or allergies:

-Sneezing

-Runny nose

-Nasal stuffiness

-Post nasal drip

-Removes inhaled irritants (dust, pollen)

-Promotes nasal and sinus drainage

-Helps reduce swelling of nasal membranes

-Moisturizes dry nasal passages

Warnings

Stop use and ask a doctor if washing is uncomfortable or

symptoms are not reduced.

When used with tap water see instructions inside box

for proper water sources.

When using this product:

- Use by only one person
- Wash with soap and water after each use
- Top rack of dishwasher safe
- Do not heat in microwave

Keep out of reach of children

Directions:

Adults and children 4 years and over: use 1 - 2 packets per 8 fl. oz (240 mL) up to every 2 hours as needed

Children under 4 years: Consult a physician

See enclosed instruction sheet for complete directions and proper use

Other information

- Inspect saline packets for integrity
- Do not use saline packets if open or torn
- Protect saline packets from excessive heat and moisture
- See saline packets or box for lot no. and expiration date

Inactive ingredients: none

Questions?

1-888-547-5492

INSTRUCTIONS FOR USE

Filter Data
Model #’s:
91-40630, 97-40630, 98-40630
Manufacturer:
Ascent Consumer Products Inc.
Melville NY 11737
888-547-5492
Distributed by:
See Box for Information
Filter Type:
Mechanical Cyst Reduction Filter
Maximum Operating Temperature:
100 degrees Fahrenheit
Maximum Working Pressure:
5 psi
Maximum Service Life:
50 gallons
This product has been tested and certified to meet NSF/ANSI Standard
53, a drinking water standard, for cyst reduction of 99.95% and to be
lead free.
For more information from the Centers for Disease Control and Prevention (CDC)
on water filters and sinus washing visit the CDC web site at: http://www.cdc.gov.
Micro-Filtered
Sinus Wash System
Please read instructions thoroughly before
using and keep for future reference.

NEW!
BUILT IN WATER
FILTER
About the Micro-Filtered Sinus Wash System
The Micro-Filtered Sinus Wash System is a revolutionary new
product that makes receiving the proven benefits of sinus
washing easier than ever. The built in water filter meets the
CDC recommendation for sinus washing with tap water*. This
provides peace of mind, while also eliminating the cost of
bottled water or the inconvenience of boiling and pre-filtering
tap water. It also allows for easier temperature control of the
saline solution for a soothing and more comfortable sinus wash

The patent pending Micro-Filtered System incorporates
additional innovations to maximize the comfort and
convenience of sinus washing:
• Inverted filter technology with anti-backflow valve uses a
combination of gravity and positive pressure to provide an
easy to control and comfortable flow of the saline solution.
• Ergonomically designed bottle and soft nasal tip are
comfortable to use and easy to clean.

Frequently asked questions and important information
about the Micro-Filtered Sinus Wash System Warning: Do not use Micro-Filtered System if nasal passages are
completely blocked.
Preparing the Micro-Filtered System for first use
Before first use rinse the bottle with warm tap water and empty. Next fill bottle
with warm tap water and place cap on bottle and tighten securely. Holding the
assembled bottle and cap over the sink, invert so comfort tip faces up and squeeze
bottle several times until bottle is empty and no water flows from the comfort tip.
Repeat the filling and emptying process two additional times. The Micro-Filtered
System is now ready for use.
What type of water can be used in the Micro-Filtered System?
In addition to distilled water or commercially bottled water the Micro-Filtered System
can be used with tap water. WARNING: The Micro-Filtered System is intended as a
final filter for tap water that is known to be safe for drinking.
How do I clean the Micro-Filtered System?
Do not clean any part of the Micro-Filtered System in the dishwasher.
Cleaning the bottle: Rinse the bottle out with water after each use and allow to dry.
Cleaning the comfort tip: Remove tip and clean with soap and water after each use.
Replace tip after cleaning.
Cleaning the cap: The outside of the cap can be rinsed with water and dried.
Can I share the Micro-Filtered System with friends and family?
The Micro-Filtered System is intended for individual use and not to be shared.

How do I clean the Micro-Filtered System?
Do not clean any part of the Micro-Filtered System in the dishwasher.
Cleaning the bottle: Rinse the bottle out with water after each use and allow to dry.
Cleaning the comfort tip: Remove tip and clean with soap and water after each use.
Replace tip after cleaning.
Cleaning the cap: The outside of the cap can be rinsed with water and dried.

Should I use an Isotonic or Hypertonic solution?
The Micro-Filtered System can be used with the enclosed saline packets to make either
an Isotonic or Hypertonic solution. An Isotonic solution has a salt concentration similar
to your body and some people find this more comfortable to use. A Hypertonic
solution is more concentrated, similar to the salt concentration of ocean water. Both
are beneficial to your sinus and nasal health.
Check with the guide below or consult with your physician for best use.

Check with the guide below or consult with your physician for best use.
Isotonic Solution1 Saline Packet per
8 fl oz
Hypertonic Solution
2 Saline Packets per
8 fl oz
Helpful hints for a more comfortable sinus wash experience:
• Begin using the Micro-Filtered System slowly – especially with children. A full
bottle of solution is not necessary to receive the full benefit.
• If the solution is too warm or too cold, the Sinus Wash will be uncomfortable.
• If stinging or irritation occurs, try using 1 packet of dry ingredients per
bottle. Gradually work up to using the solution at full strength using 2 full packets
per bottle. Do not use less than 1 packet.
• If you experience ear discomfort after use, try to blow your nose gently after the
wash. If the problem persists, the openings of your Eustachian tubes may be
particularly wide and use of the system should be discontinued.
• Breathe continuously through the mouth when using the Sinus Wash System to
avoid solution draining from the back of the nose into the mouth.

Instructions for Use:
1. Wash your hands and make sure the Micro-Filtered System has been prepared
according to the instructions above before first use.
2. Pour the contents of the saline packet(s) into the bottle. First-time users should start
with 1 packet to make an Isotonic solution. As you become more accustomed to
using the system, you may work up to using 2 full packets for a Hypertonic solution.
Additional packets may be purchased online or from your nearest pharmacy.
3. Fill the bottle with warm tap water to the 8 oz mark indicated on the bottle. Test
water temperature before using.
7. In a few moments the solution will begin to drain out of the left nostril. Continue to
squeeze the bottle gently until you have used approximately half of the solution.
8. Remove the comfort tip from your nostril, then exhale through both nostrils to clear
them of excess mucus and solution. Gently blow your nose into a tissue.
9. Repeat the procedure on the left nostril with the remaining solution.
10. When finished hold the system inverted over sink and squeeze several times to
remove solution remaining in cap.
11. Holding the cap assembly over the sink unscrew filter (B) by turning the white ring on bottom
of cap counter clockwise while holding cap (A). Empty any remaining solution into the sink
and allow to dry. Reassemble the filter making sure the black O-ring (C) is seated above the
filter base threads as shown in the illustration below. After each use please clean system.
Clean the bottle: Rinse the bottle out with water and allow to dry.
Clean the comfort tip: Remove tip and clean with soap and water and reinstall.
Clean the cap: The outside of the cap can be rinsed with water and dried.